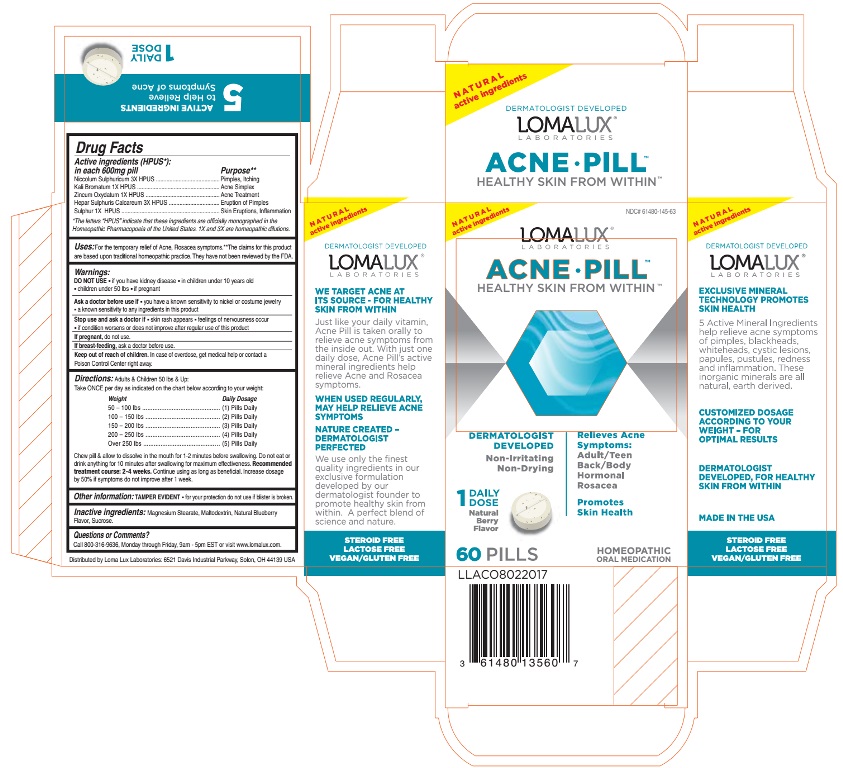 DRUG LABEL: ACNE
NDC: 61480-145 | Form: TABLET, CHEWABLE
Manufacturer: PLYMOUTH HEALTHCARE PRODUCTS LLC
Category: homeopathic | Type: HUMAN OTC DRUG LABEL
Date: 20251120

ACTIVE INGREDIENTS: NICKEL SULFATE HEXAHYDRATE 3 [hp_X]/1 1; POTASSIUM BROMIDE 1 [hp_X]/1 1; ZINC OXIDE 1 [hp_X]/1 1; CALCIUM SULFIDE 3 [hp_X]/1 1; SULFUR 1 [hp_X]/1 1
INACTIVE INGREDIENTS: SUCROSE; MALTODEXTRIN; BLUEBERRY; MAGNESIUM STEARATE

ACNE PILL

Drug Facts
Active ingredients (HPUS*) in each 600mg pill | Purpose**
Niccolum Sulphuricum 3X HPUS | Pimples, Itching
Kali Bromatum 1X HPUS | Acne Simplex
Zincum Oxydatum 1X HPUS | Acne Treatment
Hepar Sulphuris Calcareum 3X HPUS | Eruption of Pimples
Sulphur 1X HPUS | Skin Eruptions, Inflammation

*The letters "HPUS" indicate that these ingredients are officially monographed in the Homeopathic Pharmacopoeia of the United States. 1X and 3X are homeopathic dilutions.

INDICATIONS AND USAGE

Uses:For the temporary relief of Acne, Rosacea symptoms. **The claims for this product are based upon traditional homeopathic practice. They have not been reviewed by the FDA.

Warnings:

DO NOT USE

- if you have kidney disease
- in children under 10 years old
- children under 50 lbs
- if pregnant

Ask a doctor before use if

- you have a known sensitivity to nickel or costume jewelry
- a known sensitivity to any ingredients in this product

Stop use and ask a doctor if

- skin rash appears
- feelings of nervousness occur
- if condition worsens or does not improve after regular use of this product

If pregnant, do not use.

If breast-feeding, ask a doctor before use.

Keep out of reach of children.In case of overdose, get medical help or contact a Poison Control Center right away.

Keep out of reach of children.

DOSAGE AND ADMINISTRATION

Directions:Adults & Children 50 lbs & Up:

Take ONCE per day as indicated on the chart below according to your weight:

Weight Daily Dosage

50 - 100 lbs ....................... (1) Pills Daily

100 - 150 lbs ..................... (2) Pills Daily

150 - 200 lbs ..................... (3) Pills Daily

Over 200 lbs ...................... (4) Pills Daily

Chew pill & allow to dissolve in the mouth for 1-2 minutes before swallowing. Do not eat or drink anything for 10 minutes after swallowing for maximum effectiveness. Recommended treatment course: 2-4 weeks.Continue using as long as beneficial. Increase dosage by 50% if symptoms do not improve after 1 week.

Other information: TAMPER EVIDENT

- for your protection do not use if blister pack is broken.

INACTIVE INGREDIENT

Inactive ingredients:Magnesium Stearate, Maltodextrin, Natural Blueberry Flavor, Sucrose.

Questions or Comments?

Call 800-316-9636, Monday through Friday, 9am - 5pm EST or visit www.lomalux.com.

OTHER SAFETY INFORMATION

Distributed by Loma Lux Laboratories: 6521 Davis Industrial Parkway, Solon, Ohio 44139 USA

PURPOSE

Relieves Acne Symptoms:

Adult/Teen

Back/Body

Hormonal

Rosacea

Promotes Skin Health

NATURAL active ingredients

DERMATOLOGIST DEVELOPED

LOMALUX

LABORATORIES

WE TARGET ACNE AT ITS SOURCE - FOR HEALTHY SKIN FROM WITHIN

Just like your daily vitamin, Acne Pill is taken orally to relieve acne symptoms from the inside out. With just one daily dose, Acne Pill's active mineral ingredients help relieve Acne and Rosacea symptoms.

WHEN USED REGULARLY, MAY HELP RELIEVE ACNE SYMPTOMS

NATURE CREATED - DERMATOLOGIST PERFECTED

We use only the finest quality ingredients in our exclusive formulation developed by our dermatologist founder to promote healthy skin from within. A perfect blend of science and nature.

STEROID FREE

LACTOSE FREE

VEGAN/GLUTEN FREE

NATURAL active ingredients

DERMATOLOGIST DEVELOPED

LOMALUX

LABORATORIES

EXCLUSIVE MINERAL TECHNOLOGY PROMOTES SKIN HEALTH

5 Active Mineral Ingredients help relieve acne symptoms of pimples, blackheads, whiteheads, cystic lesions, papules, pustules, redness and inflammation. These inorganic minerals are all natural, earth derived.

CUSTOMIZED DOSAGE ACCORDING TO YOUR WEIGHT - FOR OPTIMAL RESULTS

DERMATOLOGIST DEVELOPED, FOR HEALTHY SKIN FROM WITHIN

STEROID FREE

LACTOSE FREE

VEGAN/GLUTEN FREE

PACKAGE LABEL

NDC# 61480-145-63

NATURAL active ingredients

LOMALUX

LABORATORIES

ACNE • PILL™

HEALTHY SKIN FROM WITHIN™

Relieves Acne Symptoms:

Adult/Teen

Back/Body

Hormonal

Rosacea

Promotes Skin Health

HOMEOPATHIC ORAL MEDICATION

DERMATOLOGIST DEVELOPED

Non - Irritating

Non - Drying

1 DAILY DOSE

Natural Berry Flavor

60PILLS